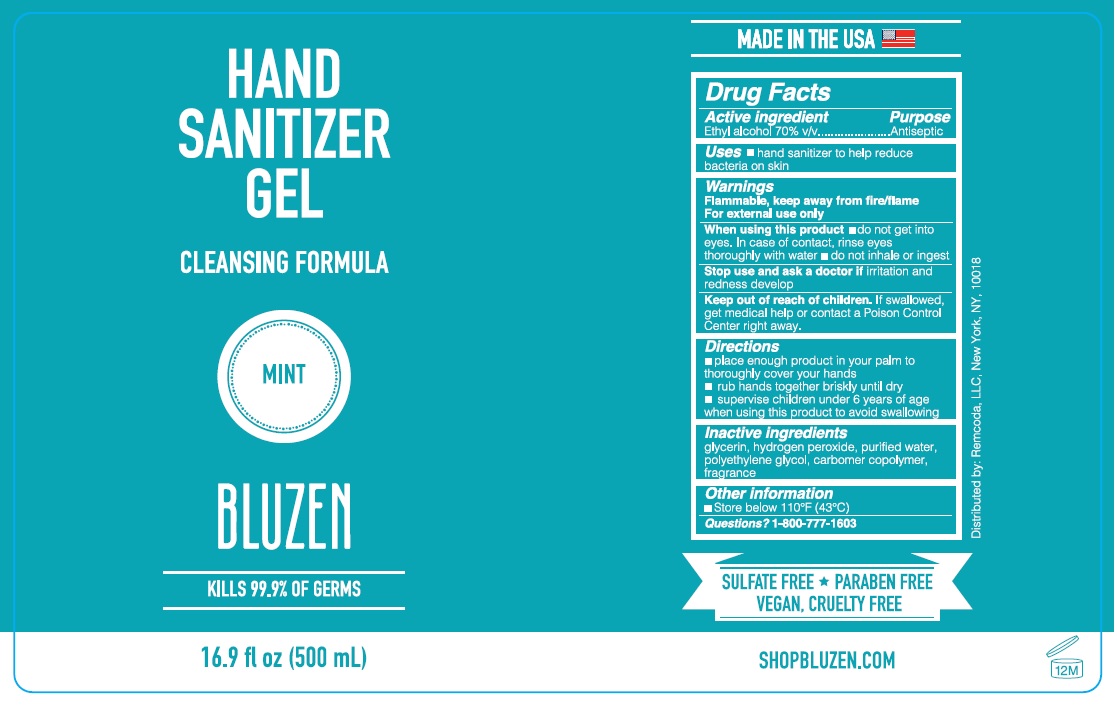 DRUG LABEL: BLUZEN HAND SANITIZER MINT
NDC: 79200-802 | Form: GEL
Manufacturer: Remcoda, Llc
Category: otc | Type: HUMAN OTC DRUG LABEL
Date: 20200911

ACTIVE INGREDIENTS: ALCOHOL 70 mL/100 mL
INACTIVE INGREDIENTS: GLYCERIN; HYDROGEN PEROXIDE; WATER; POLYETHYLENE GLYCOL, UNSPECIFIED; CARBOMER COPOLYMER TYPE A (ALLYL PENTAERYTHRITOL CROSSLINKED)

BLUZEN HAND SANITIZER GEL–MINT

Active ingredient

Ethyl alcohol 70% v/v

Purpose

Antiseptic

INDICATIONS AND USAGE

Uses ■ hand sanitizer to help reduce bacteria on skin

Warnings

Flammable, keep away from fire/flame

For external use only

When using this product ■ do not get into eyes. In case of contact, rinse eyes thoroughly with water

■ do not inhale or ingest

Stop use and ask a doctor if irritation and redness develop

Keep out of reach of children. If swallowed, get medical help or contact a Poison Control Center right away.

Directions

■ place enough product in your palm to thoroughly cover your hands

■ rub hands together briskly until dry

■ supervise children under 6 years of age when using this product to avoid swallowing.

Other information

■ Store below 110°F (43°C)

Inactive ingredients

glycerin, hydrogen peroxide, purified water, polyethylene glycol, carbomer copolymer, fragrance

Questions? 1-800-777-1603

CLEANSING FORMULA

KILLS 99.9% OF GERMS

MADE IN THE USA

SULFATE FREE PARABEN FREE

VEGAN, CRUELTY FREE

SHOPBLUZEN.COM

Distributed by: Remcoda, LLC, New York, NY, 10018